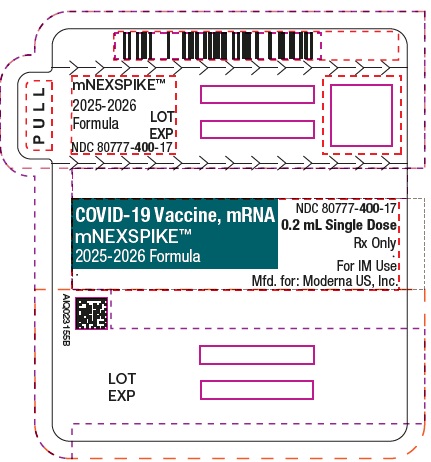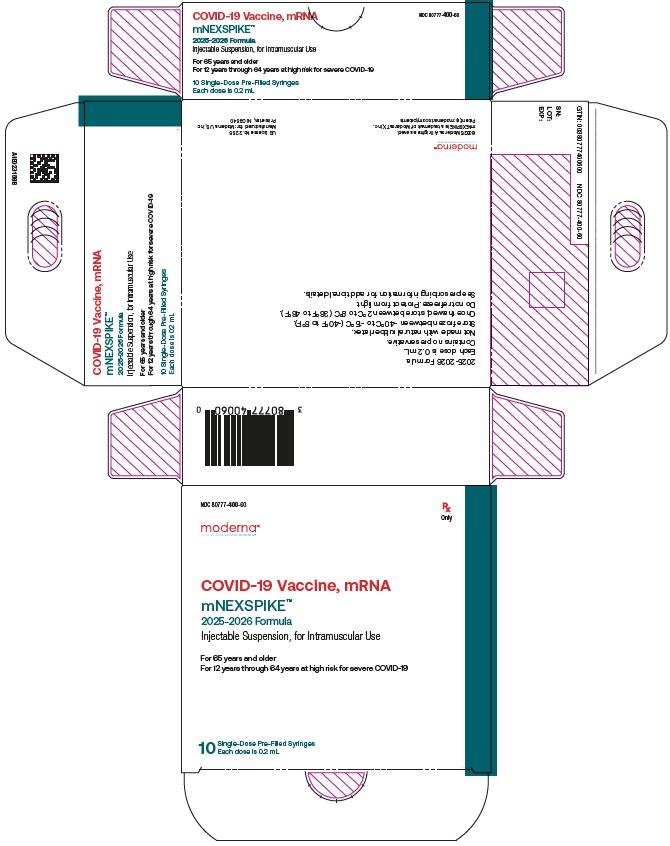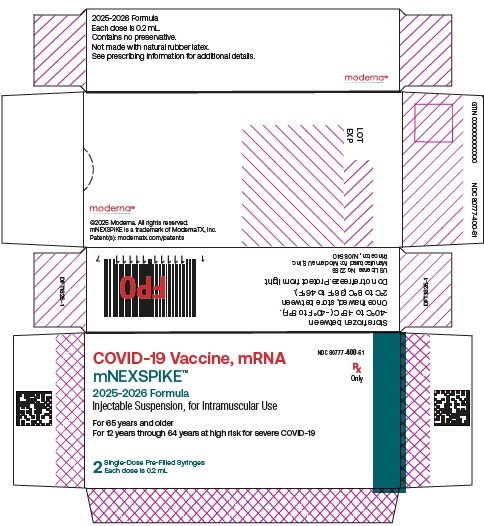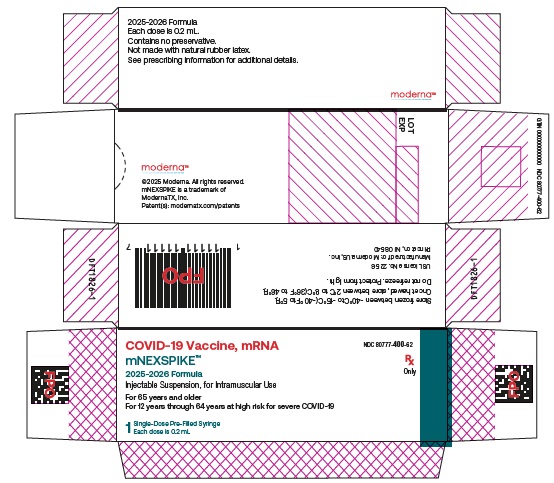 DRUG LABEL: mNEXSPIKE
NDC: 80777-400 | Form: INJECTION, SUSPENSION
Manufacturer: Moderna US, Inc.
Category: other | Type: VACCINE LABEL
Date: 20250827

ACTIVE INGREDIENTS: CX-052075 10 ug/0.2 mL
INACTIVE INGREDIENTS: SM-102; 1,2-DIMYRISTOYL-RAC-GLYCERO-3-METHOXYPOLYETHYLENE GLYCOL 2000; CHOLESTEROL; 1,2-DISTEAROYL-SN-GLYCERO-3-PHOSPHOCHOLINE; TROMETHAMINE; TROMETHAMINE HYDROCHLORIDE; SUCROSE; WATER

HIGHLIGHTS OF PRESCRIBING INFORMATION

These highlights do not include all the information needed to use MNEXSPIKE safely and effectively. See full prescribing information for MNEXSPIKE.
MNEXSPIKE (COVID-19 Vaccine, mRNA) injectable suspension, for intramuscular use
2025-2026 Formula
Initial U.S. Approval: 2025

RECENT MAJOR CHANGES

Indications and Usage (1)
Dosage and Administration,
Dosing and Schedule (2.3)
Warnings and Precautions,
Myocarditis and Pericarditis (5.2)

8/2025
8/2025
6/2025

1 INDICATIONS AND USAGE

MNEXSPIKE is a vaccine indicated for active immunization to prevent coronavirus disease 2019 (COVID-19) caused by severe acute respiratory syndrome coronavirus 2 (SARS-CoV-2).

MNEXSPIKE is approved for use in individuals who are:

- 65 years of age and older, or
- 12 years through 64 years of age with at least one underlying condition that puts them at high risk for severe outcomes from COVID-19. (1)

2 DOSAGE AND ADMINISTRATION

- For intramuscular use.
- Administer MNEXSPIKE as a single 0.2 mL dose at least 3 months after the last dose of COVID-19 vaccine. (2.3)

3 DOSAGE FORMS AND STRENGTHS

MNEXSPIKE is an injectable suspension.

A single dose is 0.2 mL. (3)

4 CONTRAINDICATIONS

Do not administer MNEXSPIKE to individuals with a known history of severe allergic reaction (e.g., anaphylaxis) to any component of MNEXSPIKE or to individuals who had a severe allergic reaction (e.g., anaphylaxis) following a previous dose of SPIKEVAX (COVID-19 Vaccine, mRNA) or any Moderna COVID-19 vaccine authorized for emergency use. (4)

5 WARNINGS AND PRECAUTIONS

Analyses of postmarketing data from use of authorized or approved mRNA COVID-19 vaccines have demonstrated increased risks of myocarditis and pericarditis, with onset of symptoms typically in the first week following vaccination. The observed risk has been highest in males 12 years through 24 years of age. (5.2)

6 ADVERSE REACTIONS

Most commonly reported adverse reactions following administration of MNEXSPIKE (≥10%):

- Participants 12 years through 17 years of age: pain at the injection site (up to 68.8%), headache (up to 54.5%), fatigue (up to 47.3%), myalgia (up to 39.2%), axillary swelling or tenderness (up to 34.6%), chills (up to 31.6%), arthralgia (up to 23.9%), and nausea/vomiting (up to 16.1%). (6)
- Participants 18 years through 64 years of age: pain at the injection site (up to 74.8%), fatigue (up to 54.3%), headache (up to 47.8%), myalgia (up to 41.6%), arthralgia (up to 32.4%), chills (up to 24.3%), axillary swelling or tenderness (up to 21.7%), and nausea/vomiting (up to 13.8%). (6)
- Participants 65 years of age and older: pain at the injection site (up to 54.6%), fatigue (up to 43.0%), headache (up to 33.1%), myalgia (up to 30.5%), arthralgia (up to 25.7%), chills (up to 16.5%), nausea/vomiting (up to 11.4%), and axillary swelling or tenderness (up to 10.7%). (6)

To report SUSPECTED ADVERSE REACTIONS, contact ModernaTX, Inc. at 1-866-663-3762 or VAERS at 1-800-822-7967 or https://vaers.hhs.gov.

FULL PRESCRIBING INFORMATION

1 INDICATIONS AND USAGE

MNEXSPIKE is a vaccine indicated for active immunization to prevent coronavirus disease 2019 (COVID-19) caused by severe acute respiratory syndrome coronavirus 2 (SARS-CoV-2).

MNEXSPIKE is approved for use in individuals who are:

- 65 years of age and older, or
- 12 years through 64 years of age with at least one underlying condition that puts them at high risk for severe outcomes from COVID-19.

2 DOSAGE AND ADMINISTRATION

For intramuscular use.

2.1 Preparation for Administration

- Verify that the label on the prefilled syringe states 2025-2026 Formula.
- If prefilled syringes of MNEXSPIKE are frozen, thaw before use following the instructions below.

Table 1: Thawing Conditions and Times
 | Thaw in; Refrigerator; 2°C to 8°C; (36°F to 46°F) | Thaw at; Room Temperature; 15°C to 25°C; (59°F to 77°F)
Carton of 10 syringes | Thaw for 2 hours and; 40 minutes | Thaw for 1 hour and; 20 minutes
Carton of 2 syringes | Thaw for 1 hour and; 40 minutes | Thaw for 40 minutes
Carton of 1 syringe | Thaw for 1 hour and; 40 minutes | Thaw for 40 minutes
One syringe (removed from carton) | Thaw for 1 hour and; 40 minutes | Thaw for 40 minutes

- After thawing, do not refreeze.
- Parenteral drug products should be inspected visually for particulate matter and discoloration prior to administration, whenever solution and container permit.
- MNEXSPIKE is a white to off-white suspension. It may contain white or translucent product-related particulates. Do not administer if vaccine is discolored or contains other particulate matter.
- Do not shake.
- With tip cap upright, remove tip cap by twisting counterclockwise until tip cap releases. Remove tip cap in a slow, steady motion. Avoid pulling tip cap while twisting.
- Attach the needle by twisting in a clockwise direction until the needle fits securely on the syringe.
- Discard after single use.

2.2 Administration

Administer MNEXSPIKE intramuscularly.

2.3 Dosing and Schedule

Administer MNEXSPIKE as a single 0.2 mL dose.

For individuals previously vaccinated with any COVID-19 vaccine, administer the dose of MNEXSPIKE at least 3 months after the last dose of COVID-19 vaccine.

3 DOSAGE FORMS AND STRENGTHS

MNEXSPIKE is an injectable suspension.

A single dose is 0.2 mL.

4 CONTRAINDICATIONS

Do not administer MNEXSPIKE to individuals with a known history of severe allergic reaction (e.g., anaphylaxis) to any component of MNEXSPIKE [see Description (11)] or to individuals who had a severe allergic reaction (e.g., anaphylaxis) following a previous dose of SPIKEVAX (COVID-19 Vaccine, mRNA) or any Moderna COVID-19 vaccine authorized for emergency use.

5 WARNINGS AND PRECAUTIONS

5.1 Management of Acute Allergic Reactions

Appropriate medical treatment must be immediately available to manage potential anaphylactic reactions following administration of MNEXSPIKE.

5.2 Myocarditis and Pericarditis

Analyses of postmarketing data from use of authorized or approved mRNA COVID-19 vaccines have demonstrated increased risks of myocarditis and pericarditis, with onset of symptoms typically in the first week following vaccination. The observed risk has been highest in males 12 years through 24 years of age.

Based on analyses of commercial health insurance claims data from inpatient and outpatient settings, the estimated unadjusted incidence of myocarditis and/or pericarditis during the period 1 through 7 days following administration of the 2023-2024 Formula of mRNA COVID-19 vaccines was approximately 8 cases per million doses in individuals 6 months through 64 years of age and approximately 27 cases per million doses in males 12 years through 24 years of age.

Although some individuals with myocarditis and/or pericarditis following administration of mRNA COVID-19 vaccines have required intensive care support, available data suggest that individuals typically have resolution of symptoms within a few days with conservative management.

Follow-up information on cardiovascular outcomes in hospitalized patients who had been diagnosed with COVID-19 vaccine-associated myocarditis is available from a longitudinal retrospective observational study. Most of these patients had received a two-dose primary series of an mRNA COVID-19 vaccine prior to their diagnosis. In this study, at a median follow-up of approximately 5 months post-vaccination, persistence of abnormal cardiac magnetic resonance imaging (CMR) findings that are a marker for myocardial injury was common. The clinical and prognostic significance of these CMR findings is not known^1 [see Adverse Reactions (6.2)].

Information is not yet available about potential long-term sequelae of myocarditis or pericarditis following administration of mRNA COVID-19 vaccines.

The Centers for Disease Control and Prevention (CDC) has published considerations related to myocarditis and pericarditis after vaccination, including for vaccination of individuals with a history of myocarditis or pericarditis (https://www.cdc.gov/vaccines/covid-19/clinical-considerations/myocarditis.html).

5.3 Syncope

Syncope (fainting) may occur in association with administration of injectable vaccines. Procedures should be in place to avoid injury from fainting.

5.4 Altered Immunocompetence

Immunocompromised persons, including individuals receiving immunosuppressive therapy, may have a diminished immune response to MNEXSPIKE [see Use in Specific Populations (8.6)].

5.5 Limitations of Vaccine Effectiveness

MNEXSPIKE may not protect all vaccine recipients.

6 ADVERSE REACTIONS

Most commonly (≥10%) reported adverse reactions following administration of MNEXSPIKE:

- Participants 12 years through 17 years of age: pain at the injection site (up to 68.8%), headache (up to 54.5%), fatigue (up to 47.3%), myalgia (up to 39.2%), axillary swelling or tenderness (up to 34.6%), chills (up to 31.6%), arthralgia (up to 23.9%), and nausea/vomiting (up to 16.1%).
- Participants 18 years through 64 years of age: pain at the injection site (up to 74.8%), fatigue (up to 54.3%), headache (up to 47.8%), myalgia (up to 41.6%), arthralgia (up to 32.4%), chills (up to 24.3%), axillary swelling or tenderness (up to 21.7%), and nausea/vomiting (up to 13.8%).
- Participants 65 years of age and older: pain at the injection site (up to 54.6%), fatigue (up to 43.0%), headache (up to 33.1%), myalgia (up to 30.5%), arthralgia (up to 25.7%), chills (16.5%), nausea/vomiting (up to 11.4%), and axillary swelling or tenderness (up to 10.7%).

6.1 Clinical Trials Experience

Because clinical trials are conducted under widely varying conditions, adverse reaction rates observed in the clinical trials of a vaccine cannot be directly compared with rates in the clinical trials of another vaccine and may not reflect the rates observed in practice.

Individuals 12 Years of Age and Older

Single Dose (Bivalent Original and Omicron BA.4/BA.5) in Vaccine-Experienced

The safety of MNEXSPIKE was evaluated in a randomized, observer-blind, active-controlled clinical trial conducted in the United States, United Kingdom, and Canada involving 11,417 participants 12 years of age and older who received a single dose of MNEXSPIKE (n=5,706) or comparator vaccine (Moderna COVID-19 Vaccine, Bivalent [Original and Omicron BA.4/BA.5] not U.S. licensed, authorized for emergency use; n=5,711) (Study 1, NCT05815498). MNEXSPIKE administered in the study contained 5 mcg mRNA encoding the membrane-bound, linked N-terminal domain (NTD) and receptor-binding domain (RBD) of the Spike (S) glycoprotein from SARS-CoV-2 Wuhan-Hu 1 strain (Original) and 5 mcg mRNA encoding the membrane-bound, linked NTD and RBD of the S glycoprotein from SARS-CoV-2 Omicron variant lineages BA.4 and BA.5. The comparator vaccine administered in the study contained 25 mcg mRNA encoding the S glycoprotein from SARS-CoV-2 Wuhan-Hu 1 strain (Original) and 25 mcg mRNA encoding the S glycoprotein from SARS-CoV-2 Omicron variant lineages BA.4 and BA.5. The median duration of follow-up for safety was 8.8 months.

In Study 1, the median age of the population was 56 years (range 12 through 96 years); 8.7% of participants were 12 years through 17 years, 62.6% were 18 years through 64 years, and 28.7% were 65 years and older. Overall, 45.7% of the participants were male, 54.3% were female, 13.2% were Hispanic or Latino, 82.2% were White, 11.2% were Black or African American, 3.6% were Asian, 0.4% were American Indian or Alaska Native, 0.1% were Native Hawaiian or Pacific Islander, 0.4% were other races, and 1.5% were Multiracial. Overall, 64.3% of study participants reported at least one CDC-defined high-risk condition for severe COVID-19. Demographic characteristics were similar between participants who received MNEXSPIKE and those who received the comparator vaccine.

All participants in the study, except one participant in the MNEXSPIKE group, had previously received at least one dose of a COVID-19 vaccine prior to the study with a median interval of 9.8 months since the last dose. Overall, 74.3% of participants (MNEXSPIKE=4,211; comparator vaccine=4,270) had evidence of prior SARS-CoV-2 infection at baseline (immunologic or virologic evidence of prior SARS-CoV-2 infection [defined as positive RT-PCR test and/or positive Elecsys immunoassay result at Day 1]).

Solicited Adverse Reactions

Local and systemic adverse reactions and use of antipyretic medication were solicited in an electronic diary for 7 days following injection (i.e., day of vaccination and the next 6 days) among participants who received MNEXSPIKE (n=5,702) and participants who received the comparator vaccine (n=5,706). Events that persisted for more than 7 days were followed until resolution.

The reported number and percentage of solicited local and systemic adverse reactions for 12 years through 17 years are presented in Table 2 and Table 3, 18 years through 64 years are presented in Table 4 and Table 5, and 65 years and older are presented in Table 6 and Table 7, respectively.

Table 2: Number and Percentage of Participants with Solicited Local Adverse Reactions Starting Within 7 Days* After Injection in Participants 12 Years Through 17 Years (Solicited Safety Set)
Local Adverse Reactionsa | MNEXSPIKEb; N=497; n; (%) | Comparator Vaccinec; N=495; n; (%)
Paind | 342; (68.8) | 390; (78.8)
Pain, Grade 3d | 10; (2.0) | 19; (3.8)
Axillary swelling or tendernessd | 172; (34.6) | 134; (27.1)
Axillary swelling or tenderness, Grade 3d | 6; (1.2) | 2; (0.4)
Swelling (hardness) ≥25 mme | 18; (3.6) | 25; (5.1)
Swelling (hardness) >100 mm, Grade 3e | 4; (0.8) | 2; (0.4)
Erythema (redness) ≥25 mme | 6; (1.2) | 13; (2.6)
* 7 days included day of vaccination and the subsequent 6 days. Events were collected in the electronic diary (e-diary).
N=Number of participants in the Solicited Safety Set.
n=Number of participants with listed solicited adverse reactions.
a Absence of rows for Grade 3 or Grade 4 adverse reactions indicates no events were reported.
b A vaccine encoding the membrane-bound, linked NTD and RBD of the S glycoprotein from SARS-CoV-2 Original and Omicron variant lineages BA.4/BA.5
c Moderna COVID-19 Vaccine, Bivalent (Original and Omicron BA.4/BA.5)
d Pain and axillary swelling or tenderness grading scale: no interference with activity (Grade 1); some interference with activity (Grade 2); prevents daily activity (Grade 3).
e Swelling and erythema grading scale: 25-50 mm / 2.5-5 cm (Grade 1); 51-100 mm / 5.1-10 cm (Grade 2); >100 mm / >10 cm (Grade 3).

Table 3: Number and Percentage of Participants with Solicited Systemic Adverse Reactions Starting Within 7 Days* After Injection in Participants 12 Years Through 17 Years (Solicited Safety Set)
Systemic Adverse Reactionsa | MNEXSPIKEb; N=497; n; (%) | Comparator Vaccinec; N=495; n; (%)
Headached | 271; (54.5) | 287; (58.0)
Headache, Grade 3d | 35; (7.0) | 20; (4.0)
Fatigued | 235; (47.3) | 251; (50.7)
Fatigue, Grade 3d | 34; (6.8) | 22; (4.4)
Myalgiad | 195; (39.2) | 178; (36.0)
Myalgia, Grade 3d | 28; (5.6) | 17; (3.4)
Chillse | 157; (31.6) | 158; (31.9)
Chills, Grade 3e | 6; (1.2) | 1; (0.2)
Arthralgiad | 119; (23.9) | 117; (23.6)
Arthralgia, Grade 3d | 10; (2.0) | 6; (1.2)
Nausea/vomitingf | 80; (16.1) | 87; (17.6)
Nausea/vomiting, Grade 3f | 0; (0) | 2; (0.4)
Feverg | 49; (9.9) | 46; (9.3)
Fever, Grade 3g | 4; (0.8) | 2; (0.4)
Use of antipyretic or pain medication | 186; (37.4) | 211; (42.6)
* 7 days included day of vaccination and the subsequent 6 days. Events and use of antipyretic or pain medication were collected in the electronic diary (e-diary).
N=Number of participants in the Solicited Safety Set.
n=Number of participants with listed solicited adverse reactions.
a No Grade 4 adverse reactions were reported.
b A vaccine encoding the membrane-bound, linked NTD and RBD of the S glycoprotein from SARS-CoV-2 Original and Omicron variant lineages BA.4/BA.5
c Moderna COVID-19 Vaccine, Bivalent (Original and Omicron BA.4/BA.5)
d Headache, fatigue, myalgia, arthralgia grading scale: no interference with activity (Grade 1); some interference with activity (Grade 2); prevents daily activity (Grade 3).
e Chills grading scale: no interference with activity (Grade 1); some interference with activity not requiring medical intervention (Grade 2); prevents daily activity and requires medical intervention (Grade 3).
f Nausea/vomiting grading scale: no interference with activity or 1-2 episodes/24 hours (Grade 1); some interference with activity or >2 episodes/24 hours (Grade 2); prevents daily activity, requires outpatient intravenous hydration (Grade 3).
g Fever grading scale: ≥38.0° – ≤38.4°C / ≥100.4° – ≤101.1°F (Grade 1); ≥38.5° – ≤38.9°C / ≥101.2°– ≤102.0°F (Grade 2); ≥39.0° – ≤40.0°C / ≥102.1° – ≤104.0°F (Grade 3).

Table 4: Number and Percentage of Participants with Solicited Local Adverse Reactions Starting Within 7 Days* After Injection in Participants 18 Years Through 64 Years (Solicited Safety Set)
Local Adverse Reactionsa | MNEXSPIKEb; N=3,573; n; (%) | Comparator Vaccinec; N=3,574; n; (%)
Paind | 2,672; (74.8) | 2,920; (81.7)
Pain, Grade 3d | 38; (1.1) | 49; (1.4)
Axillary swelling or tendernessd | 777; (21.7) | 749; (21.0)
Axillary swelling or tenderness, Grade 3d | 11; (0.3) | 15; (0.4)
Swelling (hardness) ≥25 mme | 140; (3.9) | 246; (6.9)
Swelling (hardness) >100 mm, Grade 3e | 11; (0.3) | 19; (0.5)
Erythema (redness) ≥25 mme | 85; (2.4) | 152; (4.3)
Erythema (redness) >100 mm, Grade 3e | 9; (0.3) | 17; (0.5)
* 7 days included day of vaccination and the subsequent 6 days. Events were collected in the electronic diary (e-diary).
N=Number of participants in the Solicited Safety Set.
n=Number of participants with listed solicited adverse reactions.
a No Grade 4 adverse reactions were reported.
b A vaccine encoding the membrane-bound, linked NTD and RBD of the S glycoprotein from SARS-CoV-2 Original and Omicron variant lineages BA.4/BA.5
c Moderna COVID-19 Vaccine, Bivalent (Original and Omicron BA.4/BA.5)
d Pain and axillary swelling or tenderness grading scale: no interference with activity (Grade 1); some interference with activity (Grade 2); prevents daily activity (Grade 3).
e Swelling and erythema grading scale: 25-50 mm / 2.5-5 cm (Grade 1); 51-100 mm / 5.1-10 cm (Grade 2); >100 mm / >10 cm (Grade 3).

Table 5: Number and Percentage of Participants with Solicited Systemic Adverse Reactions Starting Within 7 Days* After Injection in Participants 18 Years Through 64 Years (Solicited Safety Set)
Systemic Adverse Reactionsa | MNEXSPIKEb; N=3,573; n; (%) | Comparator Vaccinec; N=3,574; n; (%)
Fatigued | 1,939; (54.3) | 1,876; (52.5)
Fatigue, Grade 3d | 170; (4.8) | 156; (4.4)
Headached | 1,708; (47.8) | 1,583; (44.3)
Headache, Grade 3d | 90; (2.5) | 76; (2.1)
Myalgiad | 1,485; (41.6) | 1,469; (41.1)
Myalgia, Grade 3d | 144; (4.0) | 105; (2.9)
Arthralgiad | 1,159; (32.4) | 1,094; (30.6)
Arthralgia, Grade 3d | 86; (2.4) | 62; (1.7)
Chillse | 867; (24.3) | 760; (21.3)
Chills, Grade 3e | 26; (0.7) | 22; (0.6)
Nausea/vomitingf | 492; (13.8) | 424; (11.9)
Nausea/vomiting, Grade 3f | 4; (0.1) | 3; (<0.1)
Feverg | 193; (5.4) | 138; (3.9)
Fever, Grade 3g | 27; (0.8) | 17; (0.5)
Use of antipyretic or pain medication | 1,243; (34.8) | 1,226; (34.3)
* 7 days included day of vaccination and the subsequent 6 days. Events and use of antipyretic or pain medication were collected in the electronic diary (e-diary).
N=Number of participants in the Solicited Safety Set.
n=Number of participants with listed solicited adverse reactions.
a No Grade 4 adverse reactions were reported.
b A vaccine encoding the membrane-bound, linked NTD and RBD of the S glycoprotein from SARS-CoV-2 Original and Omicron variant lineages BA.4/BA.5
c Moderna COVID-19 Vaccine, Bivalent (Original and Omicron BA.4/BA.5)
d Fatigue, headache, myalgia, arthralgia grading scale: no interference with activity (Grade 1); some interference with activity (Grade 2); prevents daily activity (Grade 3).
e Chills grading scale: no interference with activity (Grade 1); some interference with activity not requiring medical intervention (Grade 2); prevents daily activity and requires medical intervention (Grade 3).
f Nausea/vomiting grading scale: no interference with activity or 1-2 episodes/24 hours (Grade 1); some interference with activity or >2 episodes/24 hours (Grade 2); prevents daily activity, requires outpatient intravenous hydration (Grade 3).
g Fever grading scale: ≥38.0° – ≤38.4°C / ≥100.4° – ≤101.1°F (Grade 1); ≥38.5° – ≤38.9°C / ≥101.2°– ≤102.0°F (Grade 2); ≥39.0° – ≤40.0°C / ≥102.1° – ≤104.0°F (Grade 3).

Table 6: Number and Percentage of Participants with Solicited Local Adverse Reactions Starting Within 7 Days* After Injection in Participants 65 Years and Older (Solicited Safety Set)
Local Adverse Reactionsa | MNEXSPIKEb; N=1,632; n; (%) | Comparator Vaccinec; N=1,637; n; (%)
Paind | 891; (54.6) | 1,109; (67.7)
Pain, Grade 3d | 12; (0.7) | 7; (0.4)
Axillary swelling or tendernessd | 174; (10.7) | 164; (10.0)
Axillary swelling or tenderness, Grade 3d | 2; (0.1) | 2; (0.1)
Swelling (hardness) ≥25 mme | 48; (2.9) | 88; (5.4)
Swelling (hardness), Grade 3e | 1; (<0.1) | 11; (0.7)
Erythema (redness) ≥25 mme | 32; (2.0) | 60; (3.7)
Erythema (redness), Grade 3e | 2; (0.1) | 7; (0.4)
* 7 days included day of vaccination and the subsequent 6 days. Events were collected in the electronic diary (e-diary).
N=Number of participants in the Solicited Safety Set.
n=Number of participants with listed solicited adverse reactions.
a No Grade 4 adverse reactions were reported.
b A vaccine encoding the membrane-bound, linked NTD and RBD of the S glycoprotein from SARS-CoV-2 Original and Omicron variant lineages BA.4/BA.5
c Moderna COVID-19 Vaccine, Bivalent (Original and Omicron BA.4/BA.5)
d Pain and axillary swelling or tenderness grading scale: no interference with activity (Grade 1); some interference with activity (Grade 2); prevents daily activity (Grade 3).
e Swelling and erythema grading scale: 25-50 mm / 2.5-5 cm (Grade 1); 51-100 mm / 5.1-10 cm (Grade 2); >100 mm / >10 cm (Grade 3).

Table 7: Number and Percentage of Participants with Solicited Systemic Adverse Reactions Starting Within 7 Days* After Injection in Participants 65 Years and Older (Solicited Safety Set)
Systemic Adverse Reactionsa | MNEXSPIKEb; N=1,632; n; (%) | Comparator Vaccinec; N=1,637; n; (%)
Fatigued | 702; (43.0) | 671; (41.0)
Fatigue, Grade 3d | 59; (3.6) | 41; (2.5)
Headached | 540; (33.1) | 479; (29.3)
Headache, Grade 3d | 22; (1.3) | 22; (1.3)
Myalgiad | 498; (30.5) | 467; (28.5)
Myalgia, Grade 3d | 33; (2.0) | 27; (1.6)
Arthralgiad | 418; (25.6) | 366; (22.4)
Arthralgia, Grade 3d | 24; (1.5) | 21; (1.3)
Chillse | 269; (16.5) | 209; (12.8)
Chills, Grade 3e | 10; (0.6) | 8; (0.5)
Nausea/vomitingf | 119; (7.3) | 114; (7.0)
Nausea/vomiting, Grade 3f | 2; (0.1) | 5; (0.3)
Feverg | 75; (4.6) | 70; (4.3)
Fever, Grade 3g | 2; (0.1) | 9; (0.6)
Fever, Grade 4g | 0; (0) | 1; (<0.1)
Use of antipyretic or pain medication | 429; (26.3) | 393; (24.0)
* 7 days included day of vaccination and the subsequent 6 days. Events and use of antipyretic or pain medication were collected in the electronic diary (e-diary).
N=Number of participants in the Solicited Safety Set.
n=Number of participants with listed solicited adverse reactions.
a Absence of rows for Grade 4 adverse reactions indicates no events were reported.
b A vaccine encoding the membrane-bound, linked NTD and RBD of the S glycoprotein from SARS-CoV-2 Original and Omicron variant lineages BA.4/BA.5
c Moderna COVID-19 Vaccine, Bivalent (Original and Omicron BA.4/BA.5)
d Headache, fatigue, myalgia, arthralgia grading scale: no interference with activity (Grade 1); some interference with activity (Grade 2); prevents daily activity (Grade 3).
e Chills grading scale: no interference with activity (Grade 1); some interference with activity not requiring medical intervention (Grade 2); prevents daily activity and requires medical intervention (Grade 3).
f Nausea/vomiting grading scale: no interference with activity or 1-2 episodes/24 hours (Grade 1); some interference with activity or >2 episodes/24 hours (Grade 2); prevents daily activity, requires outpatient intravenous hydration (Grade 3).
g Fever grading scale: ≥38.0° – ≤38.4°C / ≥100.4° – ≤101.1°F (Grade 1); ≥38.5° – ≤38.9°C / ≥101.2°– ≤102.0°F (Grade 2); ≥39.0° – ≤40.0°C / ≥102.1° – ≤104.0°F (Grade 3); >40.0°C / >104.0°F (Grade 4).

Solicited local and systemic adverse reactions reported following vaccine administration had a median duration of 2 days for MNEXSPIKE and 2 to 3 days for the comparator vaccine.

Unsolicited Adverse Events

Participants were monitored for unsolicited adverse events for 28 days following injection. Serious adverse events and medically attended adverse events will be recorded for the entire study duration (1 year). Among the 11,417 participants who received MNEXSPIKE (n=5,706) or the comparator vaccine (n=5,711), unsolicited adverse events that occurred within 28 days following injection were reported by 12.3% of participants (n=701) who received MNEXSPIKE and 11.9% of participants (n=680) who received the comparator vaccine.

There were no notable patterns or numerical imbalances between treatment groups for specific categories of adverse events that would suggest a causal relationship to MNEXSPIKE.

Serious Adverse Events

Serious adverse events were reported by 2.7% of participants (n=156) who received MNEXSPIKE and 2.6% of participants (n=151) who received the comparator vaccine through a median follow-up of 8.8 months. There were no serious adverse events considered causally related to MNEXSPIKE.

There were no notable patterns or imbalances between treatment groups for specific categories of serious adverse events that would suggest a causal relationship to MNEXSPIKE.

Single Dose (Monovalent Omicron XBB.1.5) in Vaccine-Experienced

The safety of MNEXSPIKE was evaluated in a randomized, observer-blind, active-controlled clinical trial conducted in Japan involving 689 participants 12 years of age and older who received a single dose of MNEXSPIKE (n=343) or comparator vaccine (SPIKEVAX 2023-2024 Formula [n=346]) (Study 2). MNEXSPIKE administered in the study contained 10 mcg mRNA encoding the membrane-bound, linked N-terminal domain (NTD) and receptor-binding domain (RBD) of the Spike (S) glycoprotein from SARS-CoV-2 Omicron variant lineage XBB.1.5. The comparator vaccine administered in the study contained 50 mcg mRNA encoding the S glycoprotein from SARS-CoV-2 Omicron variant lineage XBB.1.5. The median duration of follow-up for safety was 35 days.

In Study 2, the median age of the population was 52 years (range 12 through 83 years); 20.3% of participants were 12 years through 17 years, 58.8% were 18 years through 64 years, and 20.9% were 65 years of age and older. Overall, 65.7% were male, 34.3% were female, and all participants were Asian. All participants in the study had previously received at least one dose of a COVID-19 vaccine prior to the study with a median interval of 16.7 months since the last dose.

Participants were monitored for unsolicited adverse events for 28 days following injection. Among the 689 participants who received MNEXSPIKE (n=343) or the comparator vaccine (n=346), unsolicited adverse events that occurred within 28 days following injection were reported by 7.0% of participants (n=24) who received MNEXSPIKE and 6.9% of participants (n=24) who received the comparator vaccine. There were no notable patterns or numerical imbalances between treatment groups for specific categories of adverse events that would suggest a causal relationship to MNEXSPIKE. No serious adverse events were reported.

In addition, in a separate portion of Study 1, vaccine-experienced participants 12 years of age and older (n=617), including 53 participants 65 years of age and older, received a single dose of MNEXSPIKE (Monovalent Omicron XBB.1.5). Participants were monitored for serious adverse events through 6 months following injection. There were no serious adverse events considered causally related to MNEXSPIKE.

Single Dose (Monovalent Omicron XBB.1.5) in Vaccine-Naïve

In a separate randomized, observer-blind, active-controlled portion of Study 1 conducted in the United States, 782 COVID-19 vaccine-naïve participants 12 years of age and older received a single dose of MNEXSPIKE (n=396) or comparator vaccine (SPIKEVAX 2023-2024 Formula [n=386]). The vaccine formula of MNEXSPIKE administered in the study contained 10 mcg mRNA encoding the membrane-bound, linked N-terminal domain (NTD) and receptor-binding domain (RBD) of the Spike (S) glycoprotein from SARS-CoV-2 Omicron variant lineage XBB.1.5. The comparator vaccine administered in the study contained 50 mcg mRNA encoding the S glycoprotein from SARS-CoV-2 Omicron variant lineage XBB.1.5. The median duration of follow-up for safety was 5.8 months.

Among vaccine-naïve participants in this study, the median age was 38 years (range 12 through 81 years); 12.4% of participants were 12 years through 17 years, 79.4% were 18 years through 64 years, and 8.2% were 65 years and older. Overall, 46.9% of the participants were male, 53.1% were female, 36.6% were Hispanic or Latino, 53.5% were White, 42.8% were Black or African American, 0.1% were Asian, 0.9% were American Indian or Alaska Native, 0.3% were other races, and 1.5% were Multiracial. Demographic characteristics were similar between participants who received MNEXSPIKE and those who received the comparator vaccine.

Solicited Adverse Reactions

Local and systemic adverse reactions and use of antipyretic medication were solicited in an electronic diary for 7 days following injection (i.e., day of vaccination and the next 6 days) among participants who received MNEXSPIKE (n=396) and participants who received the comparator vaccine (n=386). Events that persisted for more than 7 days were followed until resolution.

The reported number and percentage of solicited local and systemic adverse reactions for vaccine-naïve participants 12 years of age and older are presented in Table 8 and Table 9.

Table 8: Number and Percentage of Participants with Solicited Local Adverse Reactions Starting Within 7 Days* After Injection in Participants 12 Years and Older (Solicited Safety Set)
Local Adverse Reactionsa | MNEXSPIKEb; N=396; n; (%) | Comparator Vaccinec; N=386; n; (%)
Paind | 145; (36.6) | 183; (47.4)
Pain, Grade 3d | 7; (1.8) | 9; (2.3)
Axillary swelling or tendernessd | 69; (17.4) | 79; (20.5)
Axillary swelling or tenderness, Grade 3d | 2; (0.5) | 4; (1.0)
Swelling (hardness) ≥25 mme | 6; (1.5) | 13; (3.4)
Swelling (hardness) >100 mm, Grade 3e | 2; (0.5) | 3; (0.8)
Erythema (redness) ≥25 mme | 5; (1.3) | 9; (2.3)
Erythema (redness) ≥100 mm, Grade 3e | 3; (0.8) | 3; (0.8)
* 7 days included day of vaccination and the subsequent 6 days. Events were collected in the electronic diary (e-diary).
N=Number of participants in the Solicited Safety Set.
n=Number of participants with listed solicited adverse reactions.
a No Grade 4 adverse reactions were reported.
b A vaccine encoding the membrane-bound, linked NTD and RBD of the S glycoprotein from SARS-CoV-2 Omicron variant lineage XBB.1.5
c SPIKEVAX 2023-2024 Formula
d Pain and axillary swelling or tenderness grading scale: no interference with activity (Grade 1); some interference with activity (Grade 2); prevents daily activity (Grade 3).
e Swelling and erythema grading scale: 25-50 mm / 2.5-5 cm (Grade 1); 51-100 mm / 5.1-10 cm (Grade 2); >100 mm / >10 cm (Grade 3).

Table 9: Number and Percentage of Participants with Solicited Systemic Adverse Reactions Starting Within 7 Days* After Injection in Participants 12 Years and Older (Solicited Safety Set)
Systemic Adverse Reactionsa | MNEXSPIKEb; N=396; n; (%) | Comparator Vaccinec; N=386; n; (%)
Headached | 119; (30.1) | 104; (26.9)
Headache, Grade 3d | 7; (1.8) | 4; (1.0)
Fatigued | 110; (27.8) | 98; (25.4)
Fatigue, Grade 3d | 10; (2.5) | 4; (1.0)
Myalgiad | 99; (25.0) | 101; (26.2)
Myalgia, Grade 3d | 10; (2.5) | 9; (2.3)
Arthralgiad | 82; (20.7) | 82; (21.2)
Arthralgia, Grade 3d | 6; (1.5) | 6; (1.6)
Chillse | 58; (14.6) | 63; (16.3)
Chills, Grade 3e | 4; (1.0) | 0; (0)
Nausea/vomitingf | 52; (13.1) | 49; (12.7)
Nausea/vomiting, Grade 3f | 2; (0.5) | 1; (0.3)
Feverg | 15; (3.8) | 11; (2.8)
Fever, Grade 3g | 4; (1.0) | 4; (1.0)
Use of antipyretic or pain medication | 84; (21.2) | 56; (14.5)
* 7 days included day of vaccination and the subsequent 6 days. Events and use of antipyretic or pain medication were collected in the electronic diary (e-diary).
N=Number of participants in the Solicited Safety Set.
n=Number of participants with listed solicited adverse reactions.
a No Grade 4 adverse reactions were reported.
b A vaccine encoding the membrane-bound, linked NTD and RBD of the S glycoprotein from SARS-CoV-2 Omicron variant lineage XBB.1.5
c SPIKEVAX 2023-2024 Formula
d Headache, fatigue, myalgia, arthralgia grading scale: no interference with activity (Grade 1); some interference with activity (Grade 2); prevents daily activity (Grade 3).
e Chills grading scale: no interference with activity (Grade 1); some interference with activity not requiring medical intervention (Grade 2); prevents daily activity and requires medical intervention (Grade 3).
f Nausea/vomiting grading scale: no interference with activity or 1-2 episodes/24 hours (Grade 1); some interference with activity or >2 episodes/24 hours (Grade 2); prevents daily activity, requires outpatient intravenous hydration (Grade 3).
g Fever grading scale: ≥38.0° – ≤38.4°C / ≥100.4° – ≤101.1°F (Grade 1); ≥38.5° – ≤38.9°C / ≥101.2°– ≤102.0°F (Grade 2); ≥39.0° – ≤40.0°C / ≥102.1° – ≤104.0°F (Grade 3).

Solicited local and systemic adverse reactions reported following vaccine administration had a median duration of 2 to 3 days for both MNEXSPIKE and the comparator vaccine. In analyses of solicited adverse reactions by age groups in vaccine-naïve participants 12 years through 17 years of age (n=51), 18 years through 64 years of age (n=310), and 65 years of age and older (n=35) who received MNEXSPIKE, the most commonly occurring solicited adverse reactions (≥10%) were reported in a similar or lower percentage of participants compared with those reported in the respective age groups in MNEXSPIKE vaccine-experienced participants (refer to Tables 2 through 7), with the exception of nausea/vomiting reported in 11.4% of vaccine-naïve participants 65 years of age and older who received MNEXSPIKE.

Unsolicited Adverse Events

Participants were monitored for unsolicited adverse events for 28 days following injection. Serious adverse events and medically attended adverse events were recorded for the entire study duration (6 months). Among the 782 vaccine-naïve participants who received MNEXSPIKE (n=396) or the comparator vaccine (n=386), unsolicited adverse events that occurred within 28 days following injection were reported by 4.3% of participants (n=17) who received MNEXSPIKE and 6.2% of participants (n=24) who received the comparator vaccine.

There were no notable patterns or numerical imbalances between treatment groups for specific categories of adverse events that would suggest a causal relationship to MNEXSPIKE.

Serious Adverse Events

Serious adverse events were reported by 1.5% of vaccine-naïve participants (n=6) who received MNEXSPIKE and 3.1% of vaccine-naïve participants (n=12) who received the comparator vaccine through a median follow-up of 5.8 months. There were no serious adverse events considered causally related to MNEXSPIKE.

There were no notable patterns or imbalances between treatment groups for specific categories of serious adverse events that would suggest a causal relationship to MNEXSPIKE.

6.2 Postmarketing Experience

Postmarketing data with authorized or approved mRNA COVID-19 vaccines have demonstrated increased risks of myocarditis and pericarditis [see Warnings and Precautions (5.2)].

Cardiovascular Outcomes in Patients Diagnosed with mRNA COVID-19 Vaccine-associated Myocarditis

In a longitudinal retrospective observational cohort study across 38 hospitals in the U.S., information on cardiovascular outcomes was collected on 333 patients 5 years through 29 years of age who had been diagnosed with COVID-19 vaccine-associated myocarditis. Among these patients, 322 were confirmed to have received an mRNA COVID-19 vaccine encoding the S glycoprotein of the Original SARS-CoV-2. Of 331 patients, 278 had onset of symptoms following the second dose of a primary series, 33 following the first dose of a primary series, and 20 following a first booster dose^1.

Among 307 patients who had been diagnosed with COVID-19 vaccine-associated myocarditis for whom follow-up information was available, 89 reported cardiac symptoms at a median follow-up of 91 days (interquartile range 25-186 days) post-vaccination^1.

Initial gadolinium-enhanced cardiac magnetic resonance imaging (CMR) was performed on 216 patients, of whom 177 had late gadolinium enhancement (LGE), a marker of myocardial injury. Among 161 patients who had LGE on initial CMR and who had a follow-up gadolinium-enhanced CMR at a median follow-up of 159 days (interquartile range 78-253 days), 98 had persistence of LGE. Overall, the severity of LGE decreased during follow-up. The clinical and prognostic significance of these CMR findings is not known^1.

Limitations of this study include potential selection bias towards patients with more severe myocarditis who are more likely to be hospitalized and have CMR, variability in diagnostic testing, and variability in follow-up^1.

8 USE IN SPECIFIC POPULATIONS

8.1 Pregnancy

Risk Summary

All pregnancies have a risk of birth defect, loss, or other adverse outcomes. In the U.S. general population, the estimated background risk of major birth defects and miscarriage in clinically recognized pregnancies is 2% to 4% and 15% to 20%, respectively. Available data on MNEXSPIKE administered to pregnant women are insufficient to inform vaccine-associated risks in pregnancy.

A developmental toxicity study was performed where female rats were administered a vaccine formulation containing 80 mcg of nucleoside-modified messenger ribonucleic acid (mRNA) (which is 8 times the amount of nucleoside-modified mRNA in a full human dose of MNEXSPIKE [encoding the N-terminal domain (NTD) and receptor-binding domain (RBD) of the spike (S) glycoprotein of SARS-CoV-2 Wuhan-Hu 1 strain]) twice prior to mating and twice during gestation. The study revealed no evidence of harm to the fetus due to the vaccine. The study also revealed no evidence of effects on female fertility (see Animal Data).

Data

Animal Data

A developmental toxicity study was conducted to assess the effects of MNEXSPIKE on pregnant/lactating female rats, as well as the development of the embryo/fetus and offspring following exposure to the female to the vaccine from implantation through the end of pregnancy, with follow-up of the offspring through weaning. In this study, 0.2 mL of a vaccine formulation containing 80 mcg of nucleoside-modified mRNA per dose (which is 8 times the amount of mRNA in a full human dose of MNEXSPIKE [10 mcg of nucleoside-modified mRNA; encoding the N-terminal domain (NTD) and receptor-binding domain (RBD) of the spike (S) glycoprotein of SARS-CoV-2 Wuhan-Hu 1 strain]). Each dose of the vaccine formulation administered to rats also contained the following ingredients: a total lipid content of 1.8 mg (SM-102, polyethylene glycol [PEG] 2000 dimyristoyl glycerol [DMG], cholesterol, and 1,2-distearoyl-sn-glycero-3-phosphocholine [DSPC]), 0.48 mg tromethamine, 17 mg sucrose, and 0.1 mg sodium acetate). MNEXSPIKE was administered to female rats by the intramuscular route on four occasions: 28 and 14 days prior to mating, and on gestation days 1 and 13. No vaccine-related fetal malformations or variations and no adverse effect on postnatal development were observed in the study. The study also revealed no evidence of effects on female fertility.

Clinical Considerations

Disease-Associated Maternal and/or Embryo/Fetal Risk

Pregnant individuals infected with SARS-CoV-2 are at increased risk of severe COVID-19 compared with non-pregnant individuals.

8.2 Lactation

Risk Summary

It is not known whether MNEXSPIKE is excreted in human milk. Data are not available to assess the effects of MNEXSPIKE on the breastfed infant or on milk production/excretion. The developmental and health benefits of breastfeeding should be considered along with the mother’s clinical need for MNEXSPIKE and any potential adverse effects on the breastfed infant from MNEXSPIKE or from the underlying maternal condition. For preventive vaccines, the underlying maternal condition is susceptibility to disease prevented by the vaccine.

8.4 Pediatric Use

Safety and effectiveness of MNEXSPIKE in individuals 12 years through 17 years of age with at least one underlying condition that puts them at high risk for severe outcomes from COVID-19 is based on safety and effectiveness data in this age group and in adults [see Adverse Reactions (6) and Clinical Studies (14)]. The safety and effectiveness of MNEXSPIKE have not been established in individuals younger than 12 years of age.

8.5 Geriatric Use

Clinical studies of MNEXSPIKE included approximately 1,801 participants 65 years of age and older and 348 participants 75 years of age and older [see Adverse Reactions (6.1) and Clinical Studies (14)].

Some local and systemic adverse reactions were reported in a lower proportion of participants 65 years of age and older compared with participants 18 years through 64 years of age [see Adverse Reactions (6.1)].

Relative vaccine efficacy was similar among participants 65 years of age and older and participants 18 years through 64 years [see Clinical Studies (14)].

8.6 Immunocompromised Individuals

The Centers for Disease Control and Prevention has published considerations related to COVID-19 vaccination for individuals who are moderately to severely immunocompromised (https://www.cdc.gov/vaccines/covid-19/clinical-considerations/covid-19-vaccines-us.html).

11 DESCRIPTION

MNEXSPIKE (COVID-19 Vaccine, mRNA) is a sterile white to off-white injectable suspension for intramuscular use.

Each 0.2 mL dose of MNEXSPIKE (2025-2026 Formula) contains 10 mcg nucleoside-modified messenger RNA (mRNA) encoding the N-terminal domain (NTD) and receptor-binding domain (RBD) of the Spike glycoprotein of the SARS-CoV-2 Omicron variant sublineage LP.8.1. Each dose also contains the following ingredients: a total lipid content of 0.2 mg (SM-102, polyethylene glycol [PEG] 2000 dimyristoyl glycerol [DMG], cholesterol, and 1,2-distearoyl-sn-glycero-3-phosphocholine [DSPC]), 0.09 mg tromethamine, 0.51 mg tromethamine hydrochloride, and 17 mg sucrose.

MNEXSPIKE does not contain a preservative.

The rubber tip cap and plunger used for the single-dose syringes are not made with natural rubber latex.

12 CLINICAL PHARMACOLOGY

12.1 Mechanism of Action

The nucleoside-modified mRNA in MNEXSPIKE is formulated in lipid particles, which enable delivery of the nucleoside-modified mRNA into host cells to allow expression of the N-terminal domain (NTD) and receptor-binding domain (RBD) of the Spike (S) glycoprotein of SARS-CoV-2. The vaccine elicits an immune response which protects against COVID-19.

13 NONCLINICAL TOXICOLOGY

13.1 Carcinogenesis, Mutagenesis, Impairment of Fertility

MNEXSPIKE has not been evaluated for the potential to cause carcinogenicity, genotoxicity, or impairment of male fertility in animals. [see Use in Specific Populations (8.1)].

14 CLINICAL STUDIES

14.1 Adults and Adolescents 12 Years of Age and Older

Efficacy and Immunogenicity of Single Dose (Bivalent Original and Omicron BA.4/BA.5) in Vaccine-Experienced

Study 1 is a Phase 3 randomized, observer-blind, active-controlled clinical trial that evaluated the relative vaccine efficacy, safety, and immunogenicity of MNEXSPIKE in participants 12 years of age and older in the United States, United Kingdom, and Canada. Randomization was stratified by age: 12 years through 17 years, 18 years through 64 years, and 65 years of age and older. The study allowed for the inclusion of participants with stable pre-existing medical conditions, defined as disease not requiring significant change in therapy or hospitalization for worsening disease during the 2 months before enrollment, as well as participants with stable human immunodeficiency virus (HIV) infection. A total of 11,454 participants were randomized in a 1:1 ratio to receive MNEXSPIKE (n=5,728), a vaccine encoding the membrane-bound, linked NTD and RBD of the S glycoprotein from SARS-CoV-2 Original and Omicron variant lineages BA.4/BA.5, or comparator vaccine (Moderna COVID-19 Vaccine, Bivalent [Original and Omicron BA.4/BA.5] not U.S. licensed, authorized for emergency use; n=5,726). All participants in the study, except one participant in the MNEXSPIKE group, had previously received at least one dose of a COVID-19 vaccine prior to the study with a median interval of 9.8 months since the last dose.

The primary efficacy analysis population (referred to as the Per-Protocol Set for Efficacy) included 11,366 participants who received either MNEXSPIKE (n=5,679) or Moderna COVID-19 Vaccine, Bivalent (n=5,687). In the Per-Protocol Set for Efficacy, 45.7% of participants were male, 54.3% were female, 13.1% were Hispanic or Latino, 82.2% were White, 11.1% were Black or African American, 3.6% were Asian, 0.4% were American Indian or Alaska Native, 0.1% were Native Hawaiian or Pacific Islander, 0.3% were other races, and 1.5% were Multiracial. The median age of participants was 56 years (range 12 through 96 years) and 28.7% of participants were 65 years of age and older. There were no notable differences in demographics between participants who received MNEXSPIKE and those who received the comparator vaccine.

The population for the relative vaccine efficacy analysis included participants 12 years of age and older who were enrolled from March 28, 2023, and followed for the development of COVID-19 through January 31, 2024. The median length of follow-up was 8 months.

The primary efficacy objective in this study was to demonstrate the noninferior vaccine efficacy against COVID-19 starting 14 days after MNEXSPIKE compared with that after the comparator vaccine. The case definition of COVID-19 was the presence of at least one symptom from a list of COVID-19 symptoms and a positive NP swab for SARS-CoV-2 by RT-PCR. Listed symptoms were fever (temperature ≥38°C / ≥100.4°F) or chills, cough, shortness of breath or difficulty breathing, fatigue, muscle aches or body aches, headache, new loss of taste or smell, sore throat, congestion or runny nose, nausea or vomiting, and diarrhea. The statistical criterion to demonstrate noninferiority (lower bound of the 99.4% CI >-10%) for relative vaccine efficacy was met (Table 10).

Table 10: Relative Vaccine Efficacy Against COVID-19* in Participants 12 Years of Age and Older† Starting 14 Days After a Single Dose of MNEXSPIKE or Comparator Vaccine – Per-Protocol Set for Efficacy
MNEXSPIKEa |  |  | Comparator Vaccineb |  |  | Relative Vaccine Efficacy; (99.4% CI)d
Participants; (N) | COVID-19; Cases; (n) | Incidence Rate of COVID-19 Per 100 Person-Monthsc | Participants; (N) | COVID-19; Cases; (n) | Incidence Rate of COVID-19 Per 100 Person-Monthsc | Relative Vaccine Efficacy; (99.4% CI)d
5,679 | 560 | 1.4 | 5,687 | 617 | 1.5 | 9.3%; (-6.6%, 22.8%)e
* Presence of at least one symptom from a list of COVID-19 symptoms and a positive NP swab for SARS-CoV-2 by RT-PCR. Listed symptoms were fever (temperature ≥38°C / ≥100.4°F) or chills, cough, shortness of breath or difficulty breathing, fatigue, muscle aches or body aches, headache, new loss of taste or smell, sore throat, congestion or runny nose, nausea or vomiting, and diarrhea.
† Participants had previously received at least one dose of a COVID-19 vaccine prior to the study.
a A vaccine encoding the membrane-bound, linked NTD and RBD of the S glycoprotein from SARS-CoV-2 Original and Omicron variant lineages BA.4/BA.5
b Moderna COVID-19 Vaccine, Bivalent (Original and Omicron BA.4/BA.5)
c Person-months is defined as the total months from study injection date to the date of event (COVID-19), date of off-study COVID-19 vaccine, last date of study participation, death date or efficacy data cutoff date, whichever is the earliest.
d Relative Vaccine Efficacy (rVE) = 1-hazard ratio (MNEXSPIKE vs comparator vaccine). Hazard ratio and CI are estimated using a stratified Cox proportional hazard model (stratified by age group per randomization) with Efron's method of tie handling and with the treatment group as a fixed effect. Alpha-adjusted 2-sided (99.4%) confidence level is calculated using Lan-DeMets O’Brien-Fleming spending function (nominal one-sided alpha = 0.0028).
e The success criterion for the primary efficacy endpoint was that the lower limit of the 2-sided CI for rVE was >-10%.

A descriptive analysis of incidence of COVID-19 in participants 12 years of age and older by age subgroup was conducted (Table 11).

Table 11: Descriptive Analysis of Incidence of COVID-19* in Participants 12 Years of Age and Older† by Age Subgroup Starting 14 Days After a Single Dose of MNEXSPIKE or Comparator Vaccine – Per-Protocol Set for Efficacy
Age Subgroup; (Years) | MNEXSPIKEa |  |  | Comparator Vaccineb |  |  | Descriptive rVEd; (95% CI)e
Age Subgroup; (Years) | Participants; (N) | COVID-19; Cases; (n) | Incidence Rate of COVID-19; Per 100 Person-Monthsc | Participants; (N) | COVID-19; Cases; (n) | Incidence Rate of COVID-19; Per 100 Person-Monthsc | Descriptive rVEd; (95% CI)e
12 to <18 | 491 | 29 | 1.0 | 490 | 23 | 0.8 | -29.2%f; (-123.3%, 25.3%)
18 to <65 | 3,558 | 382 | 1.4 | 3,562 | 422 | 1.6 | 9.7%; (-3.8%, 21.3%)
≥65 | 1,630 | 149 | 1.3 | 1,635 | 172 | 1.5 | 13.5%; (-7.7%, 30.6%)
* Presence of at least one symptom from a list of COVID-19 symptoms and a positive NP swab for SARS-CoV-2 by RT-PCR. Listed symptoms were fever (temperature ≥38°C / ≥100.4°F) or chills, cough, shortness of breath or difficulty breathing, fatigue, muscle aches or body aches, headache, new loss of taste or smell, sore throat, congestion or runny nose, nausea or vomiting, and diarrhea.
† Participants had previously received at least one dose of a COVID-19 vaccine prior to the study.
a A vaccine encoding the membrane-bound, linked NTD and RBD of the S glycoprotein from SARS-CoV-2 Original and Omicron variant lineages BA.4/BA.5
b Moderna COVID-19 Vaccine, Bivalent (Original and Omicron BA.4/BA.5)
c Person-months is defined as the total months from study injection date to the date of event (COVID-19), date of off-study COVID-19 vaccine, last date of study participation, death date or efficacy data cutoff date, whichever is the earliest.
d rVE=relative vaccine efficacy
e Descriptive relative vaccine efficacy means that these endpoints were not hypothesis-tested and do not necessarily make valid inferences about vaccine efficacy.
f VE cannot be reliably estimated due to the low number of cases accrued in this age group.

In Study 1, 60.8% of participants 12 years through 64 years of age reported at least one CDC-defined high-risk condition for severe COVID-19. The type and frequency of high-risk conditions reported in participants were generally representative of high-risk conditions in the U.S. general population 12 years through 64 years of age. A descriptive analysis of the incidence of COVID-19 in participants 12 years through 64 years of age with at least one CDC-defined high-risk condition for severe COVID-19 after a single dose of MNEXSPIKE or the comparator vaccine is presented in Table 12. In this analysis, 7.2% of participants were 12 years through 17 years of age and the remaining 92.8% of participants were 18 years through 64 years of age.

Table 12: Descriptive Analysis of Incidence of COVID-19* in Participants 12 Years Through 64 Years of Age† with at Least One CDC-Defined High-Risk Condition for Severe COVID-19‡ Starting 14 Days After a Single Dose of MNEXSPIKE or Comparator Vaccine – Per-Protocol Set for Efficacy
MNEXSPIKEa |  |  | Comparator Vaccineb |  |  | Descriptive rVEd; (95% CI)e
Participants; (N) | COVID-19; Cases; (n) | Incidence Rate of COVID-19 Per 100 Person-Monthsc | Participants; (N) | COVID-19; Cases; (n) | Incidence Rate of COVID-19 Per 100 Person-Monthsc | Descriptive rVEd; (95% CI)e
2,469 | 243 | 1.3 | 2,466 | 287 | 1.6 | 15.7%; (0, 29.0%)e
* Presence of at least one symptom from a list of COVID-19 symptoms and a positive NP swab for SARS-CoV-2 by RT-PCR. Listed symptoms were fever (temperature ≥38°C / ≥100.4°F) or chills, cough, shortness of breath or difficulty breathing, fatigue, muscle aches or body aches, headache, new loss of taste or smell, sore throat, congestion or runny nose, nausea or vomiting, and diarrhea.
† Participants had previously received at least one dose of a COVID-19 vaccine prior to the study.
‡ CDC-defined high-risk condition for severe COVID-19: https://www.cdc.gov/covid/hcp/clinical-care/underlying-conditions.html
a A vaccine encoding the membrane-bound, linked NTD and RBD of the S glycoprotein from SARS-CoV-2 Original and Omicron variant lineages BA.4/BA.5
b Moderna COVID-19 Vaccine, Bivalent (Original and Omicron BA.4/BA.5)
c Person-months is defined as the total months from study injection date to the date of event (COVID-19), date of off-study COVID-19 vaccine, last date of study participation, death date or efficacy data cutoff date, whichever is the earliest.
d Descriptive relative Vaccine Efficacy (rVE) = 1-hazard ratio (MNEXSPIKE vs comparator vaccine). Hazard ratio and CI are estimated using a stratified Cox proportional hazard model (stratified by age group per randomization) with Efron's method of tie handling and with the treatment group as a fixed effect.
e Descriptive relative vaccine efficacy means that these endpoints were not hypothesis-tested and do not necessarily make valid inferences about vaccine efficacy.

The primary immunogenicity analysis population included 621 participants who received MNEXSPIKE and 568 participants who received the comparator vaccine. Among participants assessed for immunogenicity, 45.3% were male, 54.7% were female, 13.5% were Hispanic or Latino, 80.7% were White, 11.9% were Black or African American, 4.0% were Asian, <0.1% were American Indian or Alaska Native, <0.1% were Native Hawaiian or Pacific Islander, 0.3% were other races, and 2.1% were Multiracial.

The primary immunogenicity analyses evaluated the ratio of neutralizing antibody geometric mean concentrations (GMC) and the difference in seroresponse rate (SRR) against a pseudovirus expressing Omicron BA.4/BA.5 and the original SARS-CoV-2 Spike protein (D614G) following vaccination with MNEXSPIKE compared with vaccination with the comparator vaccine.

MNEXSPIKE met the pre-specified noninferiority criterion of the lower bound of the 95% CI of GMC ratio >0.667, and the pre-specified noninferiority criterion of the lower bound of the 95% CI of the SRR-difference >-10%. These analyses are summarized in Table 13 and Table 15. Descriptive analyses of GMC and SRR by age subgroup are summarized in Table 14 and Table 16.

Table 13: Comparison of Geometric Mean Concentration 28 Days After a Single Dose of MNEXSPIKE vs 28 Days After a Single Dose of Comparator Vaccine – Per-Protocol Immunogenicity Subset*
Assaya | MNEXSPIKEb; GMC; N=621; (95% CI)c | Comparator Vaccined; GMC; N=568; (95% CI)c | GMC Ratio; (MNEXSPIKE/ Comparator Vaccine); (95% CI)c
Omicron BA.4/BA.5 | 2340.9; (2167.0, 2528.8) | 1753.8; (1618.2, 1900.7) | 1.3; (1.2, 1.5)
Original SARS-CoV-2 (D614G) | 10631.9; (9960.2, 11348.9) | 8576.5; (8012.5, 9180.1) | 1.2; (1.1, 1.4)
N=Number of participants with non-missing data at the corresponding timepoint(s).
* Per-Protocol Immunogenicity Subset included a randomly selected subset of subjects (Immunogenicity Subset) who received study vaccine, did not have a major protocol deviation that impacted immune response, and had both pre-dose and post-dose immunogenicity assessment at timepoint of primary interest (28 days post-dose). Participants had previously received at least one dose of a COVID-19 vaccine prior to the study.
a Geometric mean concentration (GMC) was determined using a SARS-CoV-2 Spike-Pseudotyped Virus Neutralization Assay. Quantification of SARS-CoV-2 neutralizing antibodies utilizes SARS-CoV-2 Reporter Virus Particles which express GFP for quantitative measurement of infection by counting the number of green fluorescent cells (assay readout [count] is Foci Forming Units [FFUs]). The serum antibody concentration (Ab[C]) of the neutralizing antibodies was determined by interpolating the mean of the replicate FFU values off the fitted reference standard curve (AU/mL).
b A vaccine encoding the membrane-bound, linked NTD and RBD of the S glycoprotein from SARS-CoV-2 Original and Omicron variant lineages BA.4/BA.5
c The log-transformed antibody levels are analyzed using an analysis of covariance (ANCOVA) model with the group variable (MNEXSPIKE vs comparator vaccine) as fixed effect, adjusted by SARS-CoV-2 infection status at baseline, randomization age group, number of prior COVID-19 boosters (0, 1, 2, ≥3), and type of last prior COVID-19 vaccine. Coefficients for Least Square Means use margins by level. The resulted LS means, difference of LS means, and 95% CI are back transformed to the original scale for presentation.
d Moderna COVID-19 Vaccine, Bivalent (Original and Omicron BA.4/BA.5)
Note: Antibody values < the lower limit of quantitation (LLOQ) are replaced by 0.5 × LLOQ. Values > the upper limit of quantitation (ULOQ) are replaced by the ULOQ if actual values are not available.

Table 14: Descriptive Analysis of Geometric Mean Concentration by Age Subgroup 28 Days After a Single Dose of MNEXSPIKE vs 28 Days After a Single Dose of Comparator Vaccine – Per-Protocol Immunogenicity Subset*
Assaya | Age Subgroup (Years) | MNEXSPIKEb; GMC; (95% CI)c | Comparator Vaccined; GMC; (95% CI)c | GMC Ratio; (MNEXSPIKE/ Comparator Vaccine); (95% CI)c
Omicron BA.4/BA.5 | 12 to <18 | N=91; 3561.4; (3037.5, 4175.7) | N=93; 3398.9; (2908.9, 3971.4) | 1.0; (0.8, 1.3)
Omicron BA.4/BA.5 | 18 to <65 | N=378; 2120.6; (1917.3, 2345.6) | N=316; 1661.0; (1487.8, 1854.4) | 1.3; (1.1, 1.5)
Omicron BA.4/BA.5 | ≥65 | N=152; 2339.5; (1984.3, 2758.3) | N=159; 1326.8; (1130.0, 1557.7) | 1.8; (1.4, 2.2)
Original SARS-CoV-2 (D614G) | 12 to <18 | N=91; 13617.7; (12006.3, 15445.3) | N=93; 12404.3; (10966.5, 14030.6) | 1.1; (0.9, 1.3)
Original SARS-CoV-2 (D614G) | 18 to <65 | N=378; 9734.8; (8938.8, 10601.7) | N=316; 8251.3; (7517.2, 9057.1) | 1.2; (1.0, 1.3)
Original SARS-CoV-2 (D614G) | ≥65 | N=152; 11451.1; (9936.3, 13196.9) | N=159; 7463.3; (6499.4, 8570.1) | 1.5; (1.3, 1.9)
N=Number of participants in the corresponding age group.
* Per-Protocol Immunogenicity Subset included a randomly selected subset of subjects (Immunogenicity Subset) who received study vaccine, did not have a major protocol deviation that impacted immune response, and had both pre-dose and post-dose immunogenicity assessment at timepoint of primary interest (28 days post-dose). Participants had previously received at least one dose of a COVID-19 vaccine prior to the study.
a Geometric mean concentration (GMC) was determined using a SARS-CoV-2 Spike-Pseudotyped Virus Neutralization Assay. Quantification of SARS-CoV-2 neutralizing antibodies utilizes SARS-CoV-2 Reporter Virus Particles which express GFP for quantitative measurement of infection by counting the number of green fluorescent cells (assay readout [count] is Foci Forming Units [FFUs]). The serum antibody concentration (Ab[C]) of the neutralizing antibodies was determined by interpolating the mean of the replicate FFU values off the fitted reference standard curve (AU/mL).
b A vaccine encoding the membrane-bound, linked NTD and RBD of the S glycoprotein from SARS-CoV-2 Original and Omicron variant lineages BA.4/BA.5
c The log-transformed antibody levels are analyzed using an analysis of covariance (ANCOVA) model with the group variable (MNEXSPIKE vs comparator vaccine) as fixed effect, adjusted by SARS-CoV-2 infection status at baseline, number of prior COVID-19 boosters (0, 1, 2, ≥3), and type of last prior COVID-19 vaccine. Coefficients for Least Square Means use margins by level. The resulted LS means, difference of LS means, and 95% CI are back transformed to the original scale for presentation.
d Moderna COVID-19 Vaccine, Bivalent (Original and Omicron BA.4/BA.5)
Note: Antibody values < the lower limit of quantitation (LLOQ) are replaced by 0.5 × LLOQ. Values > the upper limit of quantitation (ULOQ) are replaced by the ULOQ if actual values are not available.

Table 15: Comparison of Seroresponse Rate 28 Days After a Single Dose of MNEXSPIKE vs 28 Days After a Single Dose of Comparator Vaccine – Per-Protocol Immunogenicity Subset*
Assay | MNEXSPIKEa; Seroresponse Rateb; N=621; %; (95% CI)c | Comparator Vaccined; Seroresponse Rateb; N=568; %; (95% CI)c | Difference in; Seroresponse Rate; (MNEXSPIKE-Comparator Vaccine); %; (95% CI)e
Omicron BA.4/BA.5 | 79.9; (76.5, 83.0) | 65.5; (61.4, 69.4) | 14.4; (9.3, 19.4)
Original SARS-CoV-2 (D614G) | 83.6; (80.4, 86.4) | 72.9; (69.0, 76.5) | 10.7; (6.0, 15.4)
N=Number of participants with non-missing data at the corresponding timepoint(s).
* Per-Protocol Immunogenicity Subset included a randomly selected subset of subjects (Immunogenicity Subset) who received study vaccine, did not have a major protocol deviation that impacted immune response, and had both pre-dose and post-dose immunogenicity assessment at timepoint of primary interest (28 days post-dose). Participants had previously received at least one dose of a COVID-19 vaccine prior to the study.
a A vaccine encoding the membrane-bound, linked NTD and RBD of the S glycoprotein from SARS-CoV-2 Original and Omicron variant lineages BA.4/BA.5
b Seroresponse is defined as an antibody value change from baseline below the LLOQ to ≥4 × LLOQ, or at least a 4-fold rise if baseline is ≥ LLOQ and <4 × LLOQ, or at least a 2-fold rise if baseline is ≥4 × LLOQ, where baseline refers to pre-dose.
c 95% CI is calculated using the Clopper-Pearson method.
d Moderna COVID-19 Vaccine, Bivalent (Original and Omicron BA.4/BA.5)
e 95% CI is calculated using the Miettinen-Nurminen (score) confidence limits.

Table 16: Descriptive Analysis of Seroresponse Rate by Age Subgroup 28 Days After a Single Dose of MNEXSPIKE vs 28 Days After a Single Dose of Comparator Vaccine – Per-Protocol Immunogenicity Subset*
Assay | Age Subgroup; (Years) | MNEXSPIKEa; Seroresponse Rateb; %; (95% CI)c | Comparator Vaccined; Seroresponse Rateb; %; (95% CI)c | Difference in; Seroresponse Rate; (MNEXSPIKE-Comparator Vaccine); %; (95% CI)e
Omicron BA.4/BA.5 | 12 to <18 | N=91; 87.9; (79.4, 93.8) | N=93; 80.6; (71.1, 88.1) | 7.3; (-3.4, 18.0)
Omicron BA.4/BA.5 | 18 to <65 | N=378; 79.6; (75.2, 83.6) | N=316; 63.6; (58.0, 68.9) | 16.0; (9.3, 22.7)
Omicron BA.4/BA.5 | ≥65 | N=152; 75.7; (68.0, 82.2) | N=159; 60.4; (52.3, 68.0) | 15.3; (4.9, 25.3)
Original SARS-CoV-2 (D614G) | 12 to <18 | N=91; 85.7; (76.8, 92.2) | N=93; 74.2; (64.1, 82.7) | 11.5; (-0.1, 23.1)
Original SARS-CoV-2 (D614G) | 18 to <65 | N=378; 83.1; (78.9, 86.7) | N=316; 75.9; (70.8, 80.6) | 7.1; (1.1, 13.2)
Original SARS-CoV-2 (D614G) | ≥65 | N=152; 83.6; (76.7, 89.1) | N=159; 66.0; (58.1, 73.4) | 17.5; (8.0, 26.9)
N=Number of participants in the corresponding age group.
* Per-Protocol Immunogenicity Subset included a randomly selected subset of subjects (Immunogenicity Subset) who received study vaccine, did not have a major protocol deviation that impacted immune response, and had both pre-dose and post-dose immunogenicity assessment at timepoint of primary interest (28 days post-dose). Participants had previously received at least one dose of a COVID-19 vaccine prior to the study.
a A vaccine encoding the membrane-bound, linked NTD and RBD of the S glycoprotein from SARS-CoV-2 Original and Omicron variant lineages BA.4/BA.5
b Seroresponse is defined as an antibody value change from baseline below the LLOQ to ≥4 × LLOQ, or at least a 4-fold rise if baseline is ≥ LLOQ and <4 × LLOQ, or at least a 2-fold rise if baseline is ≥4 × LLOQ, where baseline refers to pre-dose.
c 95% CI is calculated using the Clopper-Pearson method.
d Moderna COVID-19 Vaccine, Bivalent (Original and Omicron BA.4/BA.5)
e 95% CI is calculated using the Miettinen-Nurminen (score) confidence limits.

Immunogenicity of Single Dose (Monovalent Omicron XBB.1.5) in Vaccine-Experienced

Study 2 is a Phase 3 randomized, observer-blind, active-controlled clinical trial that evaluated the immunogenicity and safety of MNEXSPIKE in participants 12 years of age and older in Japan. Randomization was stratified by age: 12 years through 17 years, 18 years through 64 years, and 65 years of age and older. The study allowed for the inclusion of participants with stable pre-existing medical conditions, defined as disease not requiring significant change in therapy or hospitalization for worsening disease during the 2 months before enrollment, as well as participants with stable human immunodeficiency virus (HIV) infection. A total of 692 participants were randomized in a 1:1 ratio to receive MNEXSPIKE (n=344), a vaccine encoding the membrane-bound, linked NTD and RBD of the S glycoprotein from SARS-CoV-2 Omicron XBB.1.5 lineage, or comparator vaccine (SPIKEVAX 2023-2024 Formula [n=348]). All participants had previously received at least one dose of a COVID-19 vaccine prior to the study with a median interval of 16.7 months since the last dose.

The primary immunogenicity analysis population included 334 participants who received MNEXSPIKE and 334 participants who received the comparator vaccine. Among participants assessed for immunogenicity, 65.0% were male, 35.0% were female, and all participants were Asian. The median age of participants was 52 years (range 12 through 83 years) and 20.7% of participants were 65 years of age and older.

The primary immunogenicity analyses evaluated the ratio of neutralizing antibody geometric mean concentrations (GMC) against a pseudovirus expressing Omicron XBB.1.5 SARS-CoV-2 Spike protein following vaccination with MNEXSPIKE compared to vaccination with the comparator vaccine. MNEXSPIKE met the pre-specified noninferiority criterion of the lower bound of the 95% CI of the GMC ratio >0.667 (Table 17). A descriptive analysis of the difference in seroresponse rates is summarized in Table 18.

Table 17: Comparison of Geometric Mean Concentration 28 Days After a Single Dose of MNEXSPIKE vs 28 Days After a Single Dose of Comparator Vaccine – Per-Protocol Immunogenicity Set*
Assaya | MNEXSPIKEb; GMC; (95% CI)c; N=334 | Comparator Vaccined; GMC; (95% CI)c; N=334 | GMC Ratio; (MNEXSPIKE/ Comparator Vaccine); (95% CI)c
Omicron XBB.1.5 | 1757.2; (1580.1, 1954.3) | 1470.4; (1322.4, 1635.0) | 1.2; (1.0, 1.4)
N=Number of participants with non-missing data at baseline and the corresponding timepoint(s).
* Per-Protocol Immunogenicity Set included subjects who received study vaccine, did not have a major protocol deviation that impacted immune response, and had both pre-dose and post-dose immunogenicity assessment at timepoint of primary interest (28 days post-dose). Participants had previously received at least one dose of a COVID-19 vaccine prior to the study.
a Geometric mean concentration (GMC) was determined using a SARS-CoV-2 Spike-Pseudotyped Virus Neutralization Assay. Quantification of SARS-CoV-2 neutralizing antibodies utilizes SARS-CoV-2 Reporter Virus Particles which express GFP for quantitative measurement of infection by counting the number of green fluorescent cells (assay readout [count] is Foci Forming Units [FFUs]). The serum antibody concentration (Ab[C]) of the neutralizing antibodies was determined by interpolating the mean of the replicate FFU values off the fitted reference standard curve (AU/mL).
b A vaccine encoding the membrane-bound, linked NTD and RBD of the S glycoprotein from SARS-CoV-2 Omicron XBB.1.5
c The log-transformed antibody levels are analyzed using an analysis of covariance (ANCOVA) model with the group variable (MNEXSPIKE vs comparator vaccine) as fixed effect, adjusted by SARS-CoV-2 infection status at baseline, randomization age group, number of prior COVID-19 boosters (0, 1, 2, ≥3), and type of last prior COVID-19 vaccine. LS means are based on the observed margins. The resulted LS means, difference of LS means, and 95% CI are back transformed to the original scale for presentation.
d SPIKEVAX 2023-2024 Formula
Note: Antibody values < the lower limit of quantitation (LLOQ) are replaced by 0.5 × LLOQ. Values > the upper limit of quantitation (ULOQ) are replaced by the ULOQ if actual values are not available.

Table 18: Comparison of Seroresponse Rate 28 Days After a Single Dose of MNEXSPIKE vs 28 Days After a Single Dose of Comparator Vaccine – Per-Protocol Immunogenicity Set*
Assay | MNEXSPIKEa; Seroresponse Rateb; %; (95% CI)c; N=334 | Comparator Vaccined; Seroresponse Rateb; %; (95% CI)c; N=334 | Difference in; Seroresponse Rate; (MNEXSPIKE-Comparator Vaccine); %; (95% CI)e
Omicron XBB.1.5 | 92.2; (88.8, 94.9) | 86.8; (82.7, 90.3) | 5.4; (0.8, 10.2)
N=Number of participants with non-missing data at baseline and the corresponding timepoint(s).
* Per-Protocol Immunogenicity Set included subjects who received study vaccine, did not have a major protocol deviation that impacted immune response, and had both pre-dose and post-dose immunogenicity assessment at timepoint of primary interest (28 days post-dose). Participants had previously received at least one dose of a COVID-19 vaccine prior to the study.
a A vaccine encoding the membrane-bound, linked NTD and RBD of the S glycoprotein from SARS-CoV-2 Omicron XBB.1.5
b Seroresponse is defined as an antibody value change from baseline below the LLOQ to ≥4 × LLOQ, or at least a 4-fold rise if baseline is ≥ LLOQ and <4 × LLOQ, or at least a 2-fold rise if baseline is ≥4 × LLOQ, where baseline refers to pre-dose.
c 95% CI is calculated using the Clopper-Pearson method.
d SPIKEVAX 2023-2024 Formula
e 95% CI is calculated using the Miettinen-Nurminen (score) confidence limits.

Immunogenicity of Single Dose (Monovalent Omicron XBB.1.5) in Vaccine-Naïve

In a separate observer-blind, active-controlled portion of Study 1, the immunogenicity of MNEXSPIKE was evaluated in participants 12 years of age and older in the United States. The study allowed for the inclusion of participants with stable pre-existing medical conditions, defined as disease not requiring significant change in therapy or hospitalization for worsening disease during the 2 months before enrollment, as well as participants with stable human immunodeficiency virus (HIV) infection. A total of 1,056 participants (COVID-19 vaccine-naïve [n=400] and COVID-19 vaccine-experienced [n=656]) received MNEXSPIKE, a vaccine encoding the membrane-bound, linked NTD and RBD of the S glycoprotein from SARS-CoV-2 Omicron variant lineage XBB.1.5.

The immunogenicity analysis population included 371 vaccine-naïve participants and 617 vaccine-experienced participants who received MNEXSPIKE. Among vaccine-naïve participants assessed for immunogenicity, 48.2% were male, 51.8% were female, 36.4% were Hispanic or Latino, 55.3% were White, 43.1% were Black or African American, 0.5% were American Indian or Alaska Native, and 0.3% were Multiracial. The median age of participants was 38 years (range 12 through 81 years) and 8.1% of participants were 65 years of age and older. Among vaccine-experienced participants assessed for immunogenicity, 46.0% were male, 54.0% were female, 14.1% were Hispanic or Latino, 73.3% were White, 17.2% were Black or African American, 2.9% were Asian, 0.5% were American Indian or Alaska Native, 0.2% were Native Hawaiian or Pacific Islander, 0.2% were other races, and 5.7% were Multiracial. The median age of participants was 16 years (range 12 years through 83 years) and 8.6% of participants were 65 years of age and older.

Descriptive immunogenicity analyses evaluated the ratio of neutralizing antibody geometric mean concentrations (GMC) and the difference in seroresponse rate (SRR) against a pseudovirus expressing Omicron XBB.1.5 SARS-CoV-2 Spike protein following vaccination with MNEXSPIKE in vaccine-naïve participants compared with vaccine-experienced participants (Table 19 and Table 20).

Table 19: Descriptive Analysis of Geometric Mean Concentration 28 Days After a Single Dose of MNEXSPIKE in COVID-19 Vaccine-Naïve vs COVID-19 Vaccine-Experienced Participants – Per-Protocol Immunogenicity Subset*
Assayb | MNEXSPIKEa
Assayb | Vaccine-Naïve; GMC; N=371; (95% CI)c | Vaccine-Experienced; GMC; N=617; (95% CI)c | GMC Ratio; (Vaccine-Naïve/ Vaccine-Experienced); (95% CI)c
Omicron XBB.1.5 | 2934.9; (2559.3, 3365.6) | 2640.3; (2386.8, 2920.8) | 1.1; (0.9, 1.3)
N=Number of participants with non-missing data at the corresponding timepoint(s).
* Per-Protocol Immunogenicity Subset included a randomly selected subset of subjects (Immunogenicity Subset) who received study vaccine, and did not have a major protocol deviation that impacted immune response and had both pre-dose and post-dose immunogenicity assessment at timepoint of primary interest (28 days post-dose).
a A vaccine encoding the membrane-bound, linked NTD and RBD of the S glycoprotein from SARS-CoV-2 Omicron variant lineage XBB.1.5
b Geometric mean concentration (GMC) was determined using a SARS-CoV-2 Spike-Pseudotyped Virus Neutralization Assay. Quantification of SARS-CoV-2 neutralizing antibodies utilizes SARS-CoV-2 Reporter Virus Particles which express GFP for quantitative measurement of infection by counting the number of green fluorescent cells (assay readout [count] is Foci Forming Units [FFUs]). The serum antibody concentration (Ab[C]) of the neutralizing antibodies was determined by interpolating the mean of the replicate FFU values off the fitted reference standard curve (AU/mL).
c The log-transformed antibody levels are analyzed using an analysis of covariance (ANCOVA) model with the group variable (vaccine-naïve vs vaccine-experienced) as fixed effect, adjusted by randomization age group. Least Square Means use observed margins. The resulted LS means, difference of LS means, and 95% CI are back transformed to the original scale for presentation.
Note: Antibody values < the lower limit of quantitation (LLOQ) are replaced by 0.5 × LLOQ. Values > the upper limit of quantitation (ULOQ) are replaced by the ULOQ if actual values are not available.

Table 20: Descriptive Analysis of Seroresponse Rate 28 Days After a Single Dose of MNEXSPIKE in COVID-19 Vaccine-Naïve vs COVID-19 Vaccine-Experienced Participants – Per-Protocol Immunogenicity Subset*
Assay | MNEXSPIKEa
Assay | Vaccine-Naïve; Seroresponse Rateb; N=371; %; (95% CI)c | Vaccine-Experienced; Seroresponse Rateb; N=617; %; (95% CI)c | Difference in; Seroresponse Rate; (Vaccine-Naïve-Vaccine-Experienced); %; (95% CI)d
Omicron XBB.1.5 | 91.1; (87.7, 93.8) | 86.5; (83.6, 89.1) | 4.6; (0.4, 8.4)
N=Number of participants with non-missing data at the corresponding timepoint(s).
* Per-Protocol Immunogenicity Subset included a randomly selected subset of subjects (Immunogenicity Subset) who received study vaccine, and did not have a major protocol deviation that impacted immune response and had both pre-dose and post-dose immunogenicity assessment at timepoint of primary interest (28 days post-dose).
a A vaccine encoding the membrane-bound, linked NTD and RBD of the S glycoprotein from SARS-CoV-2 Omicron variant lineage XBB.1.5
b Seroresponse is defined as an antibody value change from baseline below the LLOQ to ≥4 × LLOQ, or at least a 4-fold rise if baseline is ≥ LLOQ and <4 × LLOQ, or at least a 2-fold rise if baseline is ≥4 × LLOQ, where baseline refers to pre-dose.
c 95% CI is calculated using the Clopper-Pearson method.
d 95% CI is calculated using the Miettinen-Nurminen (score) confidence limits.

15 REFERENCES

1. Jain SS, Anderson SA, Steele JM, et al. Cardiac manifestations and outcomes of COVID-19 vaccine-associated myocarditis in the young in the USA: longitudinal results from the Myocarditis After COVID Vaccination (MACiV) multicenter study. Lancet. 2024;76:1-13. https://doi.org/10.1016/j.eclinm.2024.102809

16 HOW SUPPLIED/STORAGE AND HANDLING

MNEXSPIKE (2025-2026 Formula) is supplied as follows:

NDC 80777-400-62 Carton of 1 single-dose prefilled syringe containing 1 dose of 0.2 mL (NDC 80777-400-17)
NDC 80777-400-61 Carton of 2 single-dose prefilled syringes, each syringe containing 1 dose of 0.2 mL (NDC 80777-400-17)
NDC 80777-400-60 Carton of 10 single-dose prefilled syringes, each syringe containing 1 dose of 0.2 mL (NDC 80777-400-17)

Storage

Store frozen between -40°C to -15°C (-40°F to 5°F).

During storage and after thawing, minimize exposure to room light, and avoid exposure to direct sunlight and ultraviolet light.

After thawing, MNEXSPIKE may be stored refrigerated between 2°C to 8°C (36°F to 46°F) for up to 90 days or up to the expiration date printed on the carton, whichever comes first.

After thawing, MNEXSPIKE may be stored between 8°C to 25°C (46°F to 77°F) for up to 24 hours.

Do not refreeze once thawed.

Thawed syringes can be handled in room light conditions.

Transportation of Thawed Syringes at 2°C to 8°C (36°F to 46°F)

Thawed prefilled syringes can be transported at 2°C to 8°C (36°F to 46°F) in shipping containers qualified to maintain 2°C to 8°C (36°F to 46°F). Once thawed and transported at 2°C to 8°C (36°F to 46°F), prefilled syringes should not be refrozen and should be stored at 2°C to 8°C (36°F to 46°F) until use.

17 PATIENT COUNSELING INFORMATION

Advise the vaccine recipient or caregiver to read the FDA-approved patient labeling.

Inform the vaccine recipient or caregiver of the potential benefits and risks of vaccination with MNEXSPIKE.

Instruct the vaccine recipient or caregiver to report any adverse events to their healthcare provider or to the Vaccine Adverse Event Reporting System at 1-800-822-7967 and https://vaers.hhs.gov.

Manufactured for:
Moderna US, Inc.
Princeton, NJ 08540

©2025 ModernaTX, Inc. All rights reserved.
MNEXSPIKE is a trademark of ModernaTX, Inc.
Patent(s): www.modernatx.com/patents

US Govt. License No. 2256

Revised: 8/2025

Information for Recipients and Caregivers

MNEXSPIKE (pronounced em nex' spyk)
(COVID-19 Vaccine, mRNA)
(2025-2026 Formula)

Please read this information sheet before getting MNEXSPIKE. This summary is not intended to take the place of talking with your healthcare provider. If you have questions or would like more information, please talk with your healthcare provider.

What is MNEXSPIKE?

MNEXSPIKE is a vaccine to protect against COVID-19. MNEXSPIKE is for people who are:

- 65 years of age and older, or
- 12 years through 64 years of age at high risk for severe COVID-19.

Vaccination with MNEXSPIKE may not protect all people who receive the vaccine.

MNEXSPIKE does not contain SARS-CoV-2, the virus that causes COVID-19. MNEXSPIKE cannot give you COVID-19.

Who should not get MNEXSPIKE?

You should not get MNEXSPIKE if you had:

- a severe allergic reaction after a previous dose of either MNEXSPIKE, SPIKEVAX (COVID-19 Vaccine, mRNA), or any Moderna COVID-19 vaccine.
- a severe allergic reaction to any ingredient of this vaccine (see What are the ingredients in MNEXSPIKE?)

What should I tell my healthcare provider?

Tell your healthcare provider about all of your medical conditions, including if you:

- have any allergies
- had a severe allergic reaction after receiving a previous dose of any COVID-19 vaccine
- have had myocarditis (inflammation of the heart muscle) or pericarditis (inflammation of the lining outside the heart)
- have a fever
- have a bleeding disorder or are on a blood thinner
- are immunocompromised or are on a medicine that affects your immune system
- are pregnant or plan to become pregnant
- are breastfeeding
- have received any other COVID-19 vaccine
- have ever fainted in association with an injection

How is MNEXSPIKE given?

MNEXSPIKE is given as an injection into the muscle.

What are the risks of MNEXSPIKE?

There is a very small chance that MNEXSPIKE could cause a severe allergic reaction. A severe allergic reaction would usually occur within a few minutes to 1 hour after getting a dose of MNEXSPIKE. For this reason, your healthcare provider may ask you to stay for a short time at the place where you received your vaccine. Signs of a severe allergic reaction can include:

- Trouble breathing
- Swelling of your face and throat
- A fast heartbeat
- A rash all over your body
- Dizziness and weakness

Myocarditis (inflammation of the heart muscle) and pericarditis (inflammation of the lining outside the heart) have occurred in some people who have received mRNA COVID-19 vaccines. Myocarditis and pericarditis following administration of mRNA COVID-19 vaccines have occurred most commonly in males 12 years through 24 years of age. In most of these people, symptoms began within a week following vaccination. Based on available data, estimated rates of myocarditis and/or pericarditis from 1 through 7 days after getting a dose of the 2023-2024 Formula of mRNA COVID-19 vaccines were approximately 8 cases per million doses in people 6 months through 64 years of age and approximately 27 cases per million doses in males 12 years through 24 years of age.

In most people who have had myocarditis or pericarditis after receiving an mRNA COVID-19 vaccine, symptoms have gone away a few days after receiving treatment with medicines used to reduce inflammation.

In a study, follow-up information was collected on people who developed myocarditis after receiving the original formula of a COVID-19 vaccine; most people had received an mRNA COVID-19 vaccine. Some people in the study reported having heart symptoms approximately 3 months after developing myocarditis. Some people in the study had heart MRIs (scans that show detailed images of the heart muscle) initially after developing myocarditis and again approximately 5 months later. The initial and follow-up heart MRIs commonly showed signs of injury to the heart muscle, with improvement over time in most people. It is not known if these heart MRI findings might predict long-term heart effects of myocarditis. Studies are underway to find out if there are long-term heart effects in people who have had myocarditis after receiving an mRNA COVID-19 vaccine.

You should seek medical attention right away if you or your child has any of the following symptoms after receiving MNEXSPIKE, particularly during the 2 weeks after receiving the vaccine:

- Chest pain
- Shortness of breath
- Feelings of having a fast-beating, fluttering, or pounding heart

These could be symptoms of myocarditis or pericarditis.

Side effects that have been reported in clinical trials with MNEXSPIKE include:

- Injection site reactions: pain, tenderness and swelling of the lymph nodes in the same arm of the injection, swelling (hardness), and redness.
- General side effects: fatigue, headache, muscle pain, joint pain, chills, nausea, vomiting, and fever.

These may not be all of the possible side effects of MNEXSPIKE. Ask your healthcare provider about any side effects that concern you. You may report side effects to the Vaccine Adverse Event Reporting System (VAERS) at 1-800-822-7967 or https://vaers.hhs.gov.

What if I am pregnant or breastfeeding?

If you are pregnant or breastfeeding, discuss your options with your healthcare provider.

What are the ingredients in MNEXSPIKE?

MNEXSPIKE contains the following ingredients:

- messenger ribonucleic acid (mRNA)
- lipids (SM-102, polyethylene glycol [PEG] 2000 dimyristoyl glycerol [DMG], cholesterol, and 1,2-distearoyl-sn-glycero-3-phosphocholine [DSPC])
- tromethamine
- tromethamine hydrochloride
- sucrose

MNEXSPIKE does not contain preservatives.

If you would like more information, talk to your healthcare provider or visit MNEXSPIKE.com or call 1-866-MODERNA (1-866-663-3762).

Manufactured for:
Moderna US, Inc.
Princeton, NJ 08540

©2025 Moderna. All rights reserved.
MNEXSPIKE is a trademark of ModernaTX, Inc.
Patent(s): www.modernatx.com/patents
Revised: August 2025

PACKAGE/LABEL PRINCIPAL DISPLAY PANEL

COVID-19 Vaccine, mRNA

mNEXSPIKE

2025-2026 Formula

NDC 80777-400-17

0.2 mL Single Dose

Rx Only

For IM Use

Mfd. for: Moderna, US Inc.

PACKAGE/LABEL PRINCIPAL DISPLAY PANEL

NDC 80777-400-60

Moderna

Rx Only

COVID-19 Vaccine, mRNA

mNEXSPIKE

2025-2026 Formula

Injectable Suspension, for Intramuscular Use

For 65 years and older

For 12 years through 64 years at high risk for severe COVID-19

10 Single-Dose Pre-Filled Syringes

Each dose is 0.2 mL

PACKAGE/LABEL PRINCIPAL DISPLAY PANEL

NDC 80777-400-61

Rx Only

COVID-19 Vaccine, mRNA

mNEXSPIKE

2025-2026 Formula

Injectable Suspension, for Intramuscular Use

For 65 years and older

For 12 years through 64 years at high risk for severe COVID-19

2 Single-Dose Pre-Filled Syringes

Each dose is 0.2 mL

PACKAGE/LABEL PRINCIPAL DISPLAY PANEL

NDC 80777-400-62

Rx Only

COVID-19 Vaccine, mRNA

mNEXSPIKE

2025-2026 Formula

Injectable Suspension, for Intramuscular Use

For 65 years and older

For 12 years through 64 years at high risk for severe COVID-19

1 Single-Dose Pre-Filled Syringe

Each dose is 0.2 mL